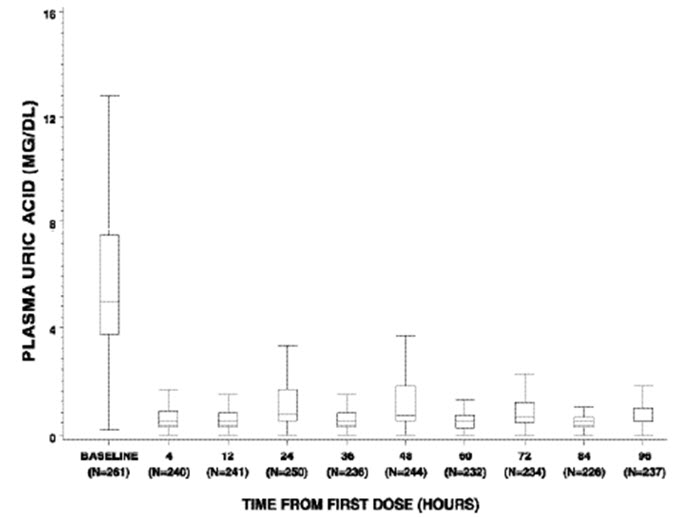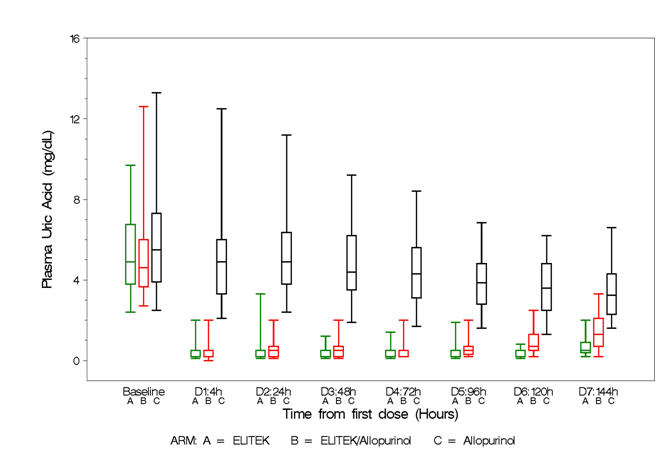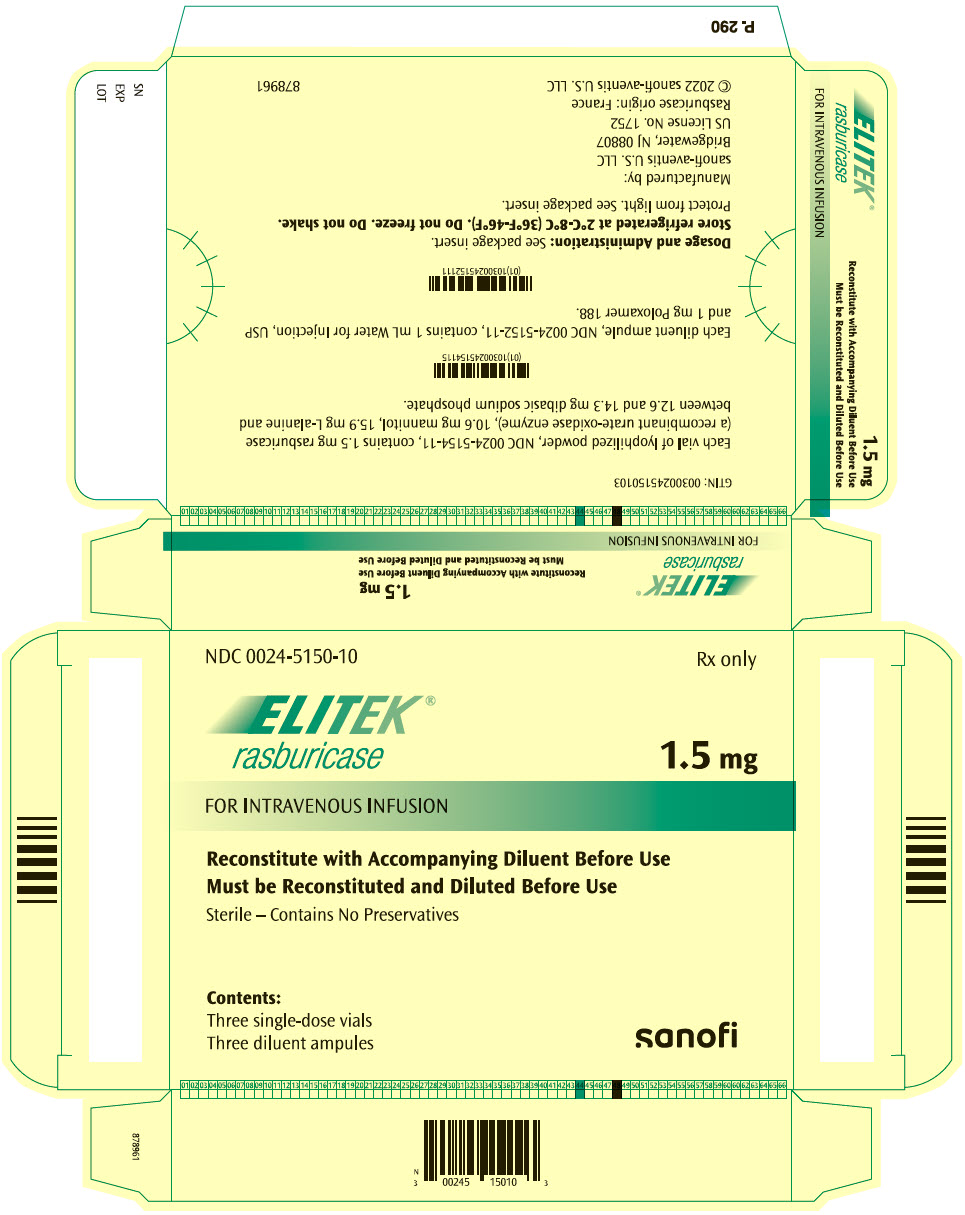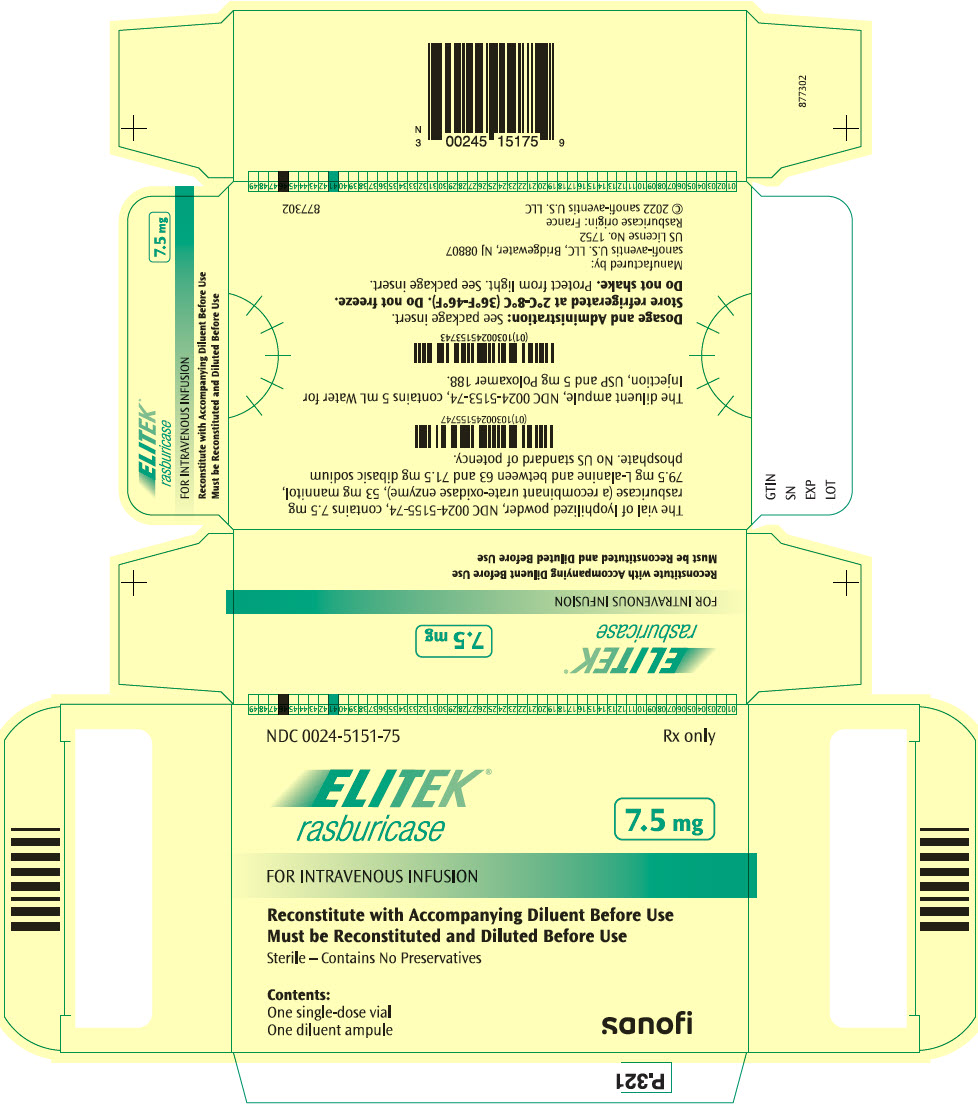 DRUG LABEL: Elitek
NDC: 0024-5150 | Form: KIT | Route: INTRAVENOUS
Manufacturer: Sanofi-Aventis U.S. LLC
Category: prescription | Type: HUMAN PRESCRIPTION DRUG LABEL
Date: 20250508

ACTIVE INGREDIENTS: RASBURICASE 1.5 mg/1 mL
INACTIVE INGREDIENTS: MANNITOL 10.6 mg/1 mL; ALANINE 15.9 mg/1 mL; SODIUM PHOSPHATE, DIBASIC, UNSPECIFIED FORM 13.45 mg/1 mL; WATER; POLOXAMER 188 1 mg/1 mL

HIGHLIGHTS OF PRESCRIBING INFORMATION

These highlights do not include all the information needed to use Elitek safely and effectively. See full prescribing information for Elitek®.
ELITEK (rasburicase) for injection, for intravenous use
Initial U.S. Approval: 2002

WARNING: HYPERSENSITIVITY REACTIONS, HEMOLYSIS, METHEMOGLOBINEMIA, AND INTERFERENCE WITH URIC ACID MEASUREMENTS

See full prescribing information for complete boxed warning.

- Hypersensitivity Reactions: Elitek can cause serious and fatal hypersensitivity reactions including anaphylaxis. Immediately and permanently discontinue Elitek if a serious hypersensitivity reaction occurs (4, 5.1, 6.2).
- Hemolysis: Do not administer Elitek to patients with glucose-6-phosphate dehydrogenase (G6PD) deficiency. Immediately and permanently discontinue Elitek if hemolysis occurs. Screen patients at higher risk for G6PD deficiency (e.g., patients of African or Mediterranean ancestry) prior to starting Elitek therapy (4, 5.2).
- Methemoglobinemia: Elitek can result in methemoglobinemia in some patients. Immediately and permanently discontinue Elitek if methemoglobinemia occurs (4, 5.3).
- Interference with uric acid measurements: Elitek enzymatically degrades uric acid in blood samples left at room temperature. Collect blood samples in prechilled tubes containing heparin and immediately immerse and maintain sample in an ice water bath. Assay plasma samples within 4 hours of collection (5.4).

1 INDICATIONS AND USAGE

Elitek is a recombinant urate-oxidase indicated for initial management of plasma uric acid levels in pediatric and adult patients with leukemia, lymphoma, and solid tumor malignancies who are receiving anticancer therapy expected to result in tumor lysis and subsequent elevation of plasma uric acid. (1)

Limitations of use: Elitek is indicated only for a single course of treatment. (1)

2 DOSAGE AND ADMINISTRATION

- Administer at 0.2 mg/kg as an intravenous infusion over 30 minutes daily for up to 5 days. (2.1)
- Do not administer as an intravenous bolus. (2.3)

3 DOSAGE FORMS AND STRENGTHS

- For injection, 1.5 mg, lyophilized powder in single-dose vial (3)
- For injection, 7.5 mg, lyophilized powder in single-dose vial (3)

4 CONTRAINDICATIONS

- History of the following reactions to rasburicase: anaphylaxis, severe hypersensitivity, hemolysis, methemoglobinemia. (4)
- Glucose-6-phosphate dehydrogenase (G6PD) deficiency. (4)

6 ADVERSE REACTIONS

Most common adverse reactions (incidence ≥20%), when used concomitantly with anticancer therapy are vomiting, nausea, fever, peripheral edema, anxiety, headache, abdominal pain, constipation, diarrhea, hypophosphatemia, pharyngolaryngeal pain, and increased alanine aminotransferase. (6.1)

To report SUSPECTED ADVERSE REACTIONS, contact sanofi-aventis U.S. LLC at 1-800-633-1610 or FDA at 1-800-FDA-1088 or www.fda.gov/medwatch.

8 USE IN SPECIFIC POPULATIONS

- Pregnancy: May cause fetal harm. (8.1)
- Lactation: Breastfeeding not recommended. (8.2)

FULL PRESCRIBING INFORMATION

WARNING: HYPERSENSITIVITY REACTIONS, HEMOLYSIS, METHEMOGLOBINEMIA, AND INTERFERENCE WITH URIC ACID MEASUREMENTS

Hypersensitivity Reactions

Elitek can cause serious and fatal hypersensitivity reactions including anaphylaxis. Immediately and permanently discontinue Elitek in patients who experience a serious hypersensitivity reaction [see Contraindications (4), Warnings and Precautions (5.1), Adverse Reactions (6.2)].

Hemolysis

Do not administer Elitek to patients with glucose-6-phosphate dehydrogenase (G6PD) deficiency. Immediately and permanently discontinue Elitek in patients developing hemolysis. Screen patients at higher risk for G6PD deficiency (e.g., patients of African or Mediterranean ancestry) prior to starting Elitek [see Contraindications (4), Warnings and Precautions (5.2)].

Methemoglobinemia

Elitek can result in methemoglobinemia in some patients. Immediately and permanently discontinue Elitek in patients developing methemoglobinemia [see Contraindications (4), Warnings and Precautions (5.3)].

Interference with Uric Acid Measurements

Elitek enzymatically degrades uric acid in blood samples left at room temperature. Collect blood samples in prechilled tubes containing heparin and immediately immerse and maintain sample in an ice water bath. Assay plasma samples within 4 hours of collection [see Warnings and Precautions (5.4)].

1 INDICATIONS AND USAGE

Elitek is indicated for the initial management of plasma uric acid levels in pediatric and adult patients with leukemia, lymphoma, and solid tumor malignancies who are receiving anticancer therapy expected to result in tumor lysis and subsequent elevation of plasma uric acid.

Limitations of Use

Elitek is indicated only for a single course of treatment [see Warnings and Precautions (5.1)].

2 DOSAGE AND ADMINISTRATION

2.1 Dosage

The recommended dose of Elitek is 0.2 mg/kg as a 30-minute intravenous infusion daily for up to 5 days. Dosing beyond 5 days or administration of more than one course is not recommended.

2.2 Reconstitution Procedure

- Elitek must be reconstituted with the diluent provided in the carton.
- Reconstitute the 1.5 mg vial of Elitek with 1 mL of diluent. Reconstitute the 7.5 mg vial of Elitek with 5 mL of diluent. Mix by swirling gently. Do not shake or vortex.
- Parenteral drug products should be inspected visually for particulate matter and discoloration prior to administration, whenever solution and container permit. Discard solution if particulate matter is visible or product is discolored.

2.3 Further Dilution and Administration

- Administer Elitek as an intravenous infusion only:
  - Inject the calculated dose of reconstituted Elitek solution into an infusion bag containing the appropriate volume of 0.9% sterile sodium chloride, to achieve a final total volume of 50 mL.
  - Infuse over 30 minutes through a separate line or flush line with at least 15 mL of normal saline prior to and after Elitek infusion.
  - Do not use filters during infusion of reconstituted Elitek drug product.
  - Store reconstituted or diluted solution at 2°C–8°C.
  - Discard unused product solution 24 hours following reconstitution.

3 DOSAGE FORMS AND STRENGTHS

- For injection: 1.5 mg, lyophilized powder in single-dose vial for reconstitution
- For injection: 7.5 mg, lyophilized powder in single-dose vial for reconstitution

4 CONTRAINDICATIONS

Elitek is contraindicated in patients with a history of anaphylaxis or severe hypersensitivity to rasburicase or in patients with development of hemolytic reactions or methemoglobinemia with rasburicase [see Boxed Warning, Warnings and Precautions (5.1, 5.2, 5.3)].

Elitek is contraindicated in individuals deficient in glucose-6-phosphate dehydrogenase (G6PD) [see Boxed Warning, Warnings and Precautions (5.2)].

5 WARNINGS AND PRECAUTIONS

5.1 Hypersensitivity Reactions

Elitek can cause serious and fatal hypersensitivity reactions including anaphylaxis. In clinical studies, anaphylaxis was reported in <1% patients receiving Elitek. This can occur at any time during treatment including the first dose. Signs and symptoms of these reactions include bronchospasm, chest pain and tightness, dyspnea, hypoxia, hypotension, shock, and urticaria. Immediately and permanently discontinue Elitek administration in any patient developing clinical evidence of a serious hypersensitivity reaction [see Boxed Warning, Contraindications (4), Adverse Reactions (6.2)].

The safety and efficacy of Elitek have been established only for a single course of treatment once daily for 5 days.

5.2 Hemolysis

Elitek is contraindicated in patients with G6PD deficiency because hydrogen peroxide is one of the major by-products of the conversion of uric acid to allantoin. In clinical studies, hemolysis occurs in <1% patients receiving Elitek; severe hemolytic reactions occurred within 2–4 days of the start of Elitek. Immediately and permanently discontinue Elitek administration in any patient developing hemolysis. Institute appropriate patient monitoring and support measures (e.g., transfusion support). Screen patients at higher risk for G6PD deficiency (e.g., patients of African or Mediterranean ancestry) prior to starting Elitek [see Boxed Warning, Contraindications (4)].

5.3 Methemoglobinemia

In clinical studies, methemoglobinemia occurred in <1% patients receiving Elitek. These included cases of serious hypoxemia requiring intervention with medical support measures. It is not known whether patients with deficiency of cytochrome b5 reductase (formerly known as methemoglobin reductase) or of other enzymes with antioxidant activity are at increased risk for methemoglobinemia or hemolytic anemia. Immediately and permanently discontinue Elitek administration in any patient identified as having developed methemoglobinemia. Institute appropriate monitoring and support measures (e.g., transfusion support, methylene-blue administration) [see Boxed Warning, Contraindications (4)].

5.4 Laboratory Test Interference

At room temperature, Elitek causes enzymatic degradation of the uric acid in blood/plasma/serum samples potentially resulting in spuriously low plasma uric acid assay readings. Special sample handling procedure must be followed to avoid ex vivo uric acid degradation [see Boxed Warning, Drug Interactions (7)].

6 ADVERSE REACTIONS

The following clinically significant adverse reactions are discussed in greater detail in other sections of the prescribing information:

- Anaphylaxis [see Boxed Warning, Contraindications (4), Warnings and Precautions (5.1)]
- Hemolysis [see Boxed Warning, Contraindications (4), Warnings and Precautions (5.2)]
- Methemoglobinemia [see Boxed Warning, Contraindications (4), Warnings and Precautions (5.3)]

6.1 Clinical Trials Experience

Because clinical trials are conducted under widely varying conditions, adverse reaction rates observed in the clinical trials of a drug cannot be directly compared to rates in the clinical trials of another drug and may not reflect the rates observed in practice.

The data below reflect exposure to Elitek in 265 pediatric and 82 adult patients enrolled in one active-controlled trial (Study 1), two uncontrolled trials (Studies 2 and 3), and an uncontrolled safety trial (n=82). Additional data were obtained from an expanded access program of 356 patients, for whom data collection was limited to serious adverse reactions. Among these 703 patients 63% were male, the median age was 10 years (range 10 days to 88 years), 73% were Caucasian, 9% African, 4% Asian, and 14% other/unknown.

Among the 347 patients for whom all adverse reactions regardless of severity were assessed, the most frequently observed adverse reactions (incidence ≥10%) were vomiting (50%), fever (46%), nausea (27%), headache (26%), abdominal pain (20%), constipation (20%), diarrhea (20%), mucositis (15%), and rash (13%). In Study 1, an active control study, the following adverse reactions occurred more frequently in Elitek-treated subjects than allopurinol-treated subjects: vomiting, fever, nausea, diarrhea, and headache. Although the incidence of rash was similar in the two arms, severe rash was reported only in one Elitek-treated patient.

Further studies, including one-active controlled study (Study 4) and four supportive studies, have been conducted in adult patients. In these studies, Elitek was administered to a total of 434 adult patients (58% male, 42% female; median age 56 years [range 18 years to 89 years]; 52% Caucasian, 7% African, 14% Asian, 28% other/unknown).

Of these 434 patients, 275 adult patients with leukemia, lymphoma, or solid tumor malignancies at risk for hyperuricemia and tumor lysis syndrome (TLS) were randomized in an open label trial receiving either Elitek alone, Elitek in combination with allopurinol, or allopurinol alone (Study 4).

A drug-related adverse reaction in Study 4 of any grade was experienced in 4.3% of Elitek-treated patients, 5.4% of Elitek/allopurinol-treated patients, and 1.1% of allopurinol-treated patients.

Table 1 presents the per-patient incidence of adverse reactions by study arm in Study 4.

Table 1: Per-Patient Incidence of Selected Adverse Reactions by Study Arm in Study 4
Adverse Reaction [Events were reported and graded according to NCI-CTC version 3.0 and presented as preferred terms MedDRA version 10.1.] | Elitek (n=92) |  | Elitek/Allopurinol (n=92) |  | Allopurinol (n=91)
Adverse Reaction [Events were reported and graded according to NCI-CTC version 3.0 and presented as preferred terms MedDRA version 10.1.] | All Grades % | Grades 3,4 % | All Grades % | Grades 3,4 % | All Grades % | Grades 3,4 %
Nausea | 57.6 | 1.1 | 60.9 | 1.1 | 54.9 | 2.2
Peripheral edema | 50 | 2.2 | 43.5 | 3.3 | 42.9 | 6.6
Vomiting | 38 | 1.1 | 37 | 0 | 30.8 | 1.1
Anxiety | 23.9 | 3.3 | 17.4 | 0 | 17.6 | 0
Abdominal pain | 21.7 | 3.3 | 33.7 | 4.3 | 25.3 | 2.2
Hypophosphatemia | 17.4 | 4.3 | 22.8 | 6.5 | 16.5 | 6.6
Hyperbilirubinemia | 16.3 | 3.3 | 14.1 | 2.2 | 7.7 | 4.4
Pharyngolaryngeal pain | 14.1 | 1.1 | 20.7 | 0 | 9.9 | 0
Sepsis | 12 | 5.4 | 7.6 | 6.5 | 4.4 | 4.4
Fluid overload | 12 | 0 | 6.5 | 0 | 3.3 | 1.1
Increased alanine aminotransferase | 10.9 | 3.3 | 27.2 | 4.3 | 17.6 | 2.2
Hyperphosphatemia | 9.8 | 0 | 15.2 | 0 | 8.8 | 1.1
Overall incidence ≥10% in any Elitek arm and the difference between any Elitek arm versus the allopurinol arm ≥5%.

Hypersensitivity reactions occurred in 4.3% of Elitek-treated patients and 1.1% of Elitek/allopurinol-treated patients in Study 4. Clinical manifestations of hypersensitivity included arthralgia, injection site irritation, peripheral edema, and rash.

The following serious adverse reactions occurred at a difference in incidence of ≥2% in patients receiving Elitek compared to patients receiving allopurinol in randomized studies (Study 1 and Study 4): pulmonary hemorrhage, respiratory failure, supraventricular arrhythmias, ischemic coronary artery disorders, and abdominal and gastrointestinal infections.

The incidence of anaphylaxis, hemolysis, and methemoglobinemia was less than 1% of the 887 Elitek-treated patients entered on these clinical trials.

6.2 Immunogenicity

As with all therapeutic proteins, there is potential for immunogenicity. Elitek can elicit antiproduct antibodies that bind to rasburicase and in some instances inhibit the activity of rasburicase in vitro [see Boxed Warning, Warnings and Precautions (5.1)].

In clinical trials of pediatric patients with hematologic malignancies, 24/218 patients tested (11%) developed antibodies by day 28 following Elitek administration as assessed by qualitative ELISA.

Using quasi-quantitative immunoassays in rasburicase-naive adult patients with hematological malignancies, 47/260 (18%) patients were positive for anti-rasburicase immunoglobulin G (IgG), 21/260 (8%) patients were positive for anti-rasburicase neutralizing IgG, and 16/260 (6%) patients were positive for anti-rasburicase immunoglobulin E (IgE) from day 14 to 24 months after 5 daily doses of Elitek.

The incidence of antibody responses detected is highly dependent on the sensitivity and specificity of the assay, which have not been fully evaluated. Additionally, the observed incidence of antibody positivity in an assay may be influenced by several factors, including serum sampling, timing and methodology, concomitant medications, and underlying disease. For these reasons, comparison of the incidence of antibodies to Elitek with the incidence of antibodies to other products may be misleading.

6.3 Postmarketing Experience

The following adverse reactions have been identified from clinical trials and/or postmarketing surveillance. Because they are reported from a population of unknown size, it is not always possible to reliably estimate their frequency or establish a causal relationship to drug exposure.

Central nervous system disorders: convulsion, muscle contractions involuntary.

Immune system disorders: cases of anaphylaxis with fatal outcome have been reported.

7 DRUG INTERACTIONS

Laboratory Test Interference

At room temperature, Elitek causes enzymatic degradation of the uric acid in blood/plasma/serum samples potentially resulting in spuriously low plasma uric acid assay readings. The following special sample handling procedure must be followed to avoid ex vivo uric acid degradation.

Uric acid must be analyzed in plasma. Blood must be collected into prechilled tubes containing heparin anticoagulant. Immediately immerse plasma samples for uric acid measurement in an ice water bath. Plasma samples must be prepared by centrifugation in a precooled centrifuge (4°C). Finally, the plasma must be maintained in an ice water bath and analyzed for uric acid within four hours of collection [see Boxed Warning].

Rasburicase does not metabolize allopurinol, cytarabine, methylprednisolone, methotrexate, 6-mercaptopurine, thioguanine, etoposide, daunorubicin, cyclophosphamide or vincristine in vitro. No metabolic-based drug interactions are therefore anticipated with these agents in patients.

8 USE IN SPECIFIC POPULATIONS

8.1 Pregnancy

Risk Summary

Based on findings in animals, Elitek may cause fetal harm when administered to pregnant women. In animal reproduction studies, intravenous administration of rasburicase to pregnant rabbits during organogenesis at 5-times the human exposure (based on AUC) at the recommended human dose of 0.2 mg/kg resulted in adverse developmental outcomes, including structural abnormalities, embryo-fetal mortality, and alterations to growth (see Data). The limited available data with Elitek use in pregnant women are insufficient to inform a drug-associated risk of major birth defects, miscarriage, or adverse maternal fetal outcomes. Consider the benefits and risks of Elitek and possible risks to the fetus when prescribing Elitek to a pregnant woman.

The estimated background risk of major birth defects and miscarriage in the indicated population is unknown. All pregnancies have a background risk of birth defect, miscarriage, or other adverse outcomes. In the U.S. general population, the estimated background risk of major birth defects and miscarriages in clinically recognized pregnancies is 2% to 4% and 15% to 20%, respectively.

Data

Animal data

Intravenous administration of rasburicase at doses of 10, 20, or 50 mg/kg/day (approximately 14, 34, and 100 times the exposure at the recommended human dose of 0.2 mg/kg) to pregnant rats from gestation days (GD) 6 to 17 produced multiple heart and great vessel malformations at 50 mg/kg/day (approximately 100 times the exposure at the recommended human dose). Intravenous administration of rasburicase from GD 6 to 19 at doses of 2, 10, or 20 mg/kg/day (approximately 5, 26, and 54 times the exposure at the recommended human dose) to pregnant rabbits produced increased pre and postimplantation loss, abortion, decreased uterine weight, decreased fetal body weights, and heart and great vessel malformations at all dose levels.

8.2 Lactation

Risk Summary

There are no available data on the presence of rasburicase in human breast milk, the effects on the breastfed child, or the effects on milk production. Because of the potential for serious adverse reactions in the breastfed child, advise patients that breastfeeding is not recommended during treatment with Elitek, and for 2 weeks after the last dose.

8.4 Pediatric Use

The safety and effectiveness of Elitek have been established in pediatric patients ages 1 month to 17 years for initial management of plasma uric acid levels in patients with leukemia, lymphoma, and solid tumor malignancies who are receiving anticancer therapy expected to result in tumor lysis and subsequent elevation of plasma uric acid. Elitek was studied in 246 pediatric patients. There were insufficient numbers of patients between 0 and 6 months (n=7) to determine whether they respond differently than older children. Mean uric acid AUC0–96 hr was higher in children <2 years of age (n=24; 150 ± s.e. 16 mg hr/dL) than those age 2 to 17 years (n=222; 108 ± s.e. 4 mg hr/dL). Children <2 years of age had a lower rate of achieving normal uric acid concentration by 48 hours (83% [95% CI: 62, 95]) than those 2 to 17 years (93% [95% CI: 89, 95]).

8.5 Geriatric Use

Of the total number of adults treated with Elitek (n=434) in clinical studies, 30% were aged 65 and over while 8% were aged 75 and over. No overall differences in pharmacokinetics, safety, and effectiveness were observed between the elderly and younger patients.

10 OVERDOSAGE

Of the six reported cases of overdosage, five cases had no adverse events reported; nonserious adverse events in the sixth case (a single dose of 1.3 mg/kg) included decreased levels of blood potassium and blood albumin, and increased levels of carbon dioxide, blood lactate dehydrogenase, blood urea, blood phosphorus, blood sodium, and blood alkaline phosphatase. Monitor patients who receive an overdose and initiate supportive measures if required.

11 DESCRIPTION

Elitek (rasburicase) is a recombinant urate-oxidase produced by a genetically modified Saccharomyces cerevisiae strain. The cDNA coding for rasburicase was cloned from a strain of Aspergillus flavus.

Rasburicase is a tetrameric protein with identical subunits. Each subunit is made up of a single 301 amino acid polypeptide chain with a molecular mass of about 34 kDa. The drug product is a sterile, white to off-white, lyophilized powder intended for intravenous administration following reconstitution with a diluent. Elitek is supplied in 2 mL or 3 mL and 10 mL colorless, glass vials containing rasburicase at a concentration of 1.5 mg/mL after reconstitution.

Elitek 1.5 mg presentation contains 1.5 mg rasburicase, 10.6 mg mannitol, 15.9 mg L-alanine, between 12.6 and 14.3 mg of dibasic sodium phosphate (lyophilized powder), and a diluent (1 mL Water for Injection, USP, and 1 mg Poloxamer 188).

Elitek 7.5 mg presentation contains 7.5 mg of rasburicase, 53 mg mannitol, 79.5 mg L-alanine, and between 63 and 71.5 mg dibasic sodium phosphate (lyophilized powder) and a diluent (5 mL Water for Injection, USP, and 5 mg Poloxamer 188).

12 CLINICAL PHARMACOLOGY

12.1 Mechanism of Action

In humans, uric acid is the final step in the catabolic pathway of purines. Rasburicase catalyzes enzymatic oxidation of poorly soluble uric acid into an inactive and more soluble metabolite (allantoin).

12.2 Pharmacodynamics

The measurement of plasma uric acid was used to evaluate the effectiveness of rasburicase in clinical studies. Following administration of either 0.15 or 0.20 mg/kg rasburicase daily for up to 5 days, plasma uric acid levels decreased within 4 hours and were maintained below 7.5 mg/dL in 98% of adult and 90% of pediatric patients for at least 7 days. There was no evidence of a dose response effect on uric acid control for doses between 0.15 and 0.20 mg/kg rasburicase.

In preclinical in vivo studies, rasburicase did not affect the activity of isoenzymes CYP1A, CYP2A, CYP2B, CYP2C, CYP2E, and CYP3A, suggesting no induction or inhibition potential. Clinically relevant P450-mediated drug-drug interactions are therefore not anticipated in patients treated with the recommended Elitek dose and dosing schedule.

12.3 Pharmacokinetics

The pharmacokinetics of rasburicase was evaluated in both pediatric and adult patients with leukemia, lymphoma or other hematological malignancies. Rasburicase exposure, as measured by AUC0–24 hr and Cmax, tended to increase with a dose range from 0.15 to 0.2 mg/kg. The mean terminal half-life was similar between pediatric and adult patients and ranged from 15.7 to 22.5 hours. The mean volume of distribution of rasburicase ranged from 110 to 127 mL/kg in pediatric patients and from 75.8 to 138 mL/kg in adult patients, respectively. Minimal accumulation of rasburicase (<1.3-fold) was observed between days 1 and 5 of dosing. In adults, age, gender, baseline liver enzymes and creatinine clearance did not impact the pharmacokinetics of rasburicase. A cross-study comparison revealed that after administration of rasburicase at 0.15 or 0.20 mg/kg, the geometric mean values of body-weight normalized clearance were approximately 40% lower in Japanese (n=20) than that in Caucasians (n=22).

13 NONCLINICAL TOXICOLOGY

13.1 Carcinogenesis, Mutagenesis, Impairment of Fertility

Carcinogenicity studies in animals to evaluate tumorigenic potential of rasburicase have not been performed. Rasburicase was not mutagenic in the Ames, unscheduled DNA synthesis, chromosome analysis, mouse lymphoma, and micronucleus tests.

Rasburicase did not affect reproductive performance or fertility in male or female rats with an exposure 11-times greater at a dose of 10 mg/kg than the recommended human dose of 0.2 mg/kg.

14 CLINICAL STUDIES

14.1 Pediatrics

Elitek was administered in three studies to 265 patients with acute leukemia or non-Hodgkin's lymphoma. These clinical studies were largely limited to pediatric patients (246 of 265). Elitek was administered as a 30-minute infusion once (n=251) or twice (n=14) daily at a dose of 0.15 or 0.2 mg/kg/dose (total daily dose 0.2–0.4 mg/kg/day). Elitek was administered prior to and concurrent with antitumor therapy, which consisted of either systemic chemotherapy (n=196) or steroids (n=69).

Study 1

Study 1 was a randomized, open-label, controlled study conducted at six institutions, in which 52 pediatric patients were randomized to receive either Elitek (n=27) or allopurinol (n=25). The dose of allopurinol varied according to local institutional practice. Elitek was administered as an intravenous infusion over 30 minutes once (n=26) or twice (n=1) daily at a dose of 0.2 mg/kg/dose (total daily dose 0.2–0.4 mg/kg/day). Initiation of dosing was permitted at any time between 4 to 48 hours before the start of antitumor therapy and could be continued for 5 to 7 days after initiation of antitumor therapy. Patients were stratified at randomization on the basis of underlying malignant disease (leukemia or lymphoma) and baseline serum or plasma uric acid levels (<8 mg/dL and ≥8 mg/dL). The primary study objective was to demonstrate a greater reduction in uric acid concentration over 96 hours (AUC0–96 hr) in the Elitek group as compared to the allopurinol group. Uric acid AUC0–96 hr was defined as the area under the curve for plasma uric acid levels (mg hr/dL), measured from the last value prior to the first dose of Elitek until 96 hours after that first dose. Plasma uric acid levels were used for all uric acid AUC0–96 hr calculations [see Warnings and Precautions (5.4)].

The demographics of the two study arms (Elitek vs allopurinol) were as follows: age <13 years (82% vs 76%), males (59% vs 72%), Caucasian (59% vs 72%), ECOG performance status 0 (89% vs 84%), and leukemia (74% vs 76%). The median interval, in hours, between initiation of Elitek and of antitumor treatment was 20 hours, with a range of 70 hours before to 10 hours after the initiation of antitumor treatment (n=24, data not reported for 3 patients).

The uric acid AUC0–96 hr was significantly lower in the Elitek group (128 ± s.e. 14 mg hr/dL) as compared to the allopurinol group (328 ± s.e. 26 mg hr/dL). All but one patient in the Elitek arm had reduction and maintenance of uric acid levels to within or below the normal range during the treatment. The incidence of renal dysfunction was similar in the two study arms; one patient in the allopurinol arm developed acute renal failure.

Study 2

Study 2 was a multi-institutional, single-arm study conducted in 89 pediatric and 18 adult patients with hematologic malignancies. Patients received Elitek at a dose of 0.15 mg/kg/day. The primary efficacy objective was determination of the proportion of patients with maintained plasma uric acid concentration at 48 hours where maintenance of uric acid concentration was defined as: 1) achievement of uric acid concentration ≤6.5 mg/dL (patients <13 years) or ≤7.5 mg/dL (patients ≥13 years) within a designated time point (48 hours) from initiation of Elitek and maintained until 24 hours after the last administration of study drug; and 2) control of uric acid level without the need for allopurinol or other agents.

The study population demographics were: age <13 years (76%), males (61%), Caucasian (91%), ECOG performance status=0 (92%), and leukemia (89%).

The proportion of patients with maintenance of uric acid concentration at 48 hours in Study 2 was 99% (106/107).

Study 3

Study 3 was a multi-institutional, single-arm study conducted in 130 pediatric patients and 1 adult patient with hematologic malignancies. Patients received Elitek at either a dose of 0.15 mg/kg/day (n=12) or 0.2 mg/kg/day (n=119). The primary efficacy objective was determination of the proportion of patients with maintained plasma uric acid concentration at 48 hours as defined for Study 2 above.

The study population demographics were: age <13 years (76%), Caucasian (83%), males (67%), ECOG=0 (67%), and leukemia (88%).

The proportion of patients with maintenance of uric acid concentration at 48 hours in Study 3 was 92% in the 0.15 mg/kg group (n=12) and 95% in the 0.2 mg/kg group (n=119).

Pooled Analyses of Studies 1, 2, and 3

Data from the 3 studies (n=265) were pooled and analyzed according to the plasma uric acid levels over time. The pretreatment plasma uric acid concentration was ≥8 mg/dL in 61 patients and was <8 mg/dL in 200 patients. The median uric acid concentration at baseline, at 4 hours following the first dose of Elitek, and the per-patient fall in plasma uric acid concentration from baseline to 4 hours, were calculated in those patients with both pretreatment and 4-hour post-treatment values. Among patients with pretreatment uric acid ≥8 mg/dL (baseline median 10.6 mg/dL [range 8.1-36.4]), the median per-patient change in plasma uric acid concentration by 4 hours after the first dose was a decrease of 9.1 mg/dL (0.3-19.3 mg/dL). Among the patients with a pretreatment plasma uric acid level <8 mg/dL (baseline median 4.6 mg/dL [range 0.2-7.9 mg/dL]), the median per-patient change in plasma uric acid concentration by 4 hours after the first dose was a decrease of 4.1 mg/dL (0.1-7.6 mg/dL).

Figure 1: Box and Whisker Plot of Uric Acid Concentration at Designated Time Blocks – Elitek Administration Began Immediately after Baseline

Figure 1 is a box and whisker plot of plasma uric acid levels inclusive of 261 of the 265 Elitek-treated patients from Studies 1, 2, and 3. Of the 261 evaluable patients, plasma uric acid concentration was maintained (see Study 2 for the definition of uric acid concentration maintenance) by 4 hours for 92% of patients (240/261), by 24 hours for 93% of patients (245/261), by 48 hours for 97% of patients (254/261), by 72 hours for 99% of patients (260/261), and by 96 hours for 100% of patients (261/261). Of the subset of 61 patients whose plasma uric acid level was elevated at baseline (≥8 mg/dL), plasma uric acid concentration was maintained by 4 hours for 72% of patients (44/61), by 24 hours for 80% of patients (49/61), by 48 hours for 92% of patients (56/61), by 72 hours for 98% of patients (60/61), and by 96 hours for 100% (61/61).

14.2 Studies in Adults

A total of 342 adults with either leukemia, lymphoma, or other hematologic malignancy received Elitek in five studies (one randomized study, Study 4, and four uncontrolled studies). Across the five studies, Elitek was administered at a dose of 0.15 mg/kg/day (n=38) or 0.2 mg/kg/day (n=304).

Study 4 was a randomized (1:1:1), multi-center, open-label study conducted in patients with leukemia, lymphoma, and solid tumor malignancies at risk for hyperuricemia and TLS. A total of 275 adult patients received at least one dose of study drug. The median age was 56 years, 62% were males, 80% were Caucasian, 66% had leukemia, 29% had lymphoma; 18% were hyperuricemic (uric acid >7.5 mg/dL) at study entry. Patients in Arm A received Elitek for 5 days (n=92). Patients in Arm B received Elitek from day 1 through day 3 followed by oral allopurinol from day 3 through day 5 (overlap on day 3: Elitek and allopurinol administered approximately 12 hours apart) (n=92). Patients in Arm C received oral allopurinol for 5 days (n=91). Elitek was administered at the dose of 0.2 mg/kg/day as a 30-minute infusion once daily. Allopurinol was administered orally at the dose of 300 mg once a day. Patients were eligible for the study if they were either at high risk or potential risk for TLS. The major endpoint of this study was the uric acid response rate defined as the proportion of patients with plasma uric acid levels ≤7.5 mg/dL from day 3 to day 7, after initiation of antihyperuricemic treatment.

Table 2 presents the response rates in the three treatment arms. The response rate in arm A was significantly greater than in arm C (p=0.0009). The response rate was higher for arm B compared to arm C; this difference was not statistically significant.

Table 2: Summary of Response Rates
 | Arm A Elitek n=92 | Arm B Elitek/Allopurinol n=92 | Arm C Allopurinol n=91
Response Rate % (95% CI) | 87% (80%, 94%) | 78% (70%, 87%) | 66% (56%, 76%)
Nonresponse Rate % | 13% | 22% | 34%
Failed to control uric acid | 0 | 0 | 11%
Hyperuricemic treatment extended beyond 5 days | 0 | 6.5% | 4.4%
Missing uric acid samples | 13% | 15% | 19%

There were no patients with documented failure to control uric acid in arms A or B. In arm C, 34% of patients did not have a uric acid response; 11% due to failure to control uric acid and 4.4% due to the need for extended antihyperuricemic treatment.

Box and whisker plots of uric acid over time for the patient population (Figure 2) show that in the two arms containing Elitek, uric acid levels were ≤2 mg/dL in 96% of patients at 4 hours of the day 1 dose.

Figure 2: Uric Acid Concentration Over Time – Patient Population Box and Whisker Plot

Tumor Lysis Syndrome (TLS)

Clinical TLS was defined by changes in at least two or more laboratory parameters for hyperuricemia, hyperkalemia, hyperphosphatemia and hypocalcemia and at least one of the following events occurring within 7 days of treatment: renal failure/injury, need for renal dialysis, and/or serum creatinine increase >1.5 ULN, arrhythmia or seizure. Clinical TLS occurred in 3% of Elitek-treated patients, 3% of Elitek/allopurinol-treated patients, and 4% of allopurinol-treated patients.

16 HOW SUPPLIED/STORAGE AND HANDLING

How Supplied

NDC 0024-5150-10: One carton contains 3 single-dose vials each containing 1.5 mg of rasburicase and 3 ampules each containing 1 mL diluent.

NDC 0024-5151-75: One carton contains 1 single-dose vial containing 7.5 mg of rasburicase and 1 ampule containing 5 mL diluent.

Storage and Handling

The lyophilized drug product and the diluent for reconstitution should be stored at 2°C-8°C (36°F-46°F). Do not freeze. Protect from light.

17 PATIENT COUNSELING INFORMATION

Hypersensitivity Reactions

Instruct patients to notify their physician immediately if any of the following occur: allergic reaction, bronchospasm, chest pain or tightness, dyspnea, hypoxia, hypotension, shock or urticaria [see Boxed Warning, Warnings and Precautions (5.1)].

Lactation

Advise females not to breastfeed during treatment with Elitek and for at least 2 weeks after the last dose [see Use in Specific Populations (8.2)].

Manufactured by:
sanofi-aventis U.S. LLC
Morristown, NJ 07960
U.S. License No. 1752

©2025 sanofi-aventis U.S. LLC

PRINCIPAL DISPLAY PANEL - 1.5 mg Kit Carton

NDC 0024-5150-10
Rx only

ELITEK®
rasburicase

1.5 mg

FOR INTRAVENOUS INFUSION

Reconstitute with Accompanying Diluent Before Use
Must be Reconstituted and Diluted Before Use

Sterile – Contains No Preservatives

Contents:
Three single-dose vials
Three diluent ampules

sanofi

PRINCIPAL DISPLAY PANEL - 7.5 mg Kit Carton

NDC 0024-5151-75
Rx only

ELITEK®
rasburicase

7.5 mg

FOR INTRAVENOUS INFUSION

Reconstitute with Accompanying Diluent Before Use
Must be Reconstituted and Diluted Before Use

Sterile – Contains No Preservatives

Contents:
One single-dose vial
One diluent ampule

sanofi